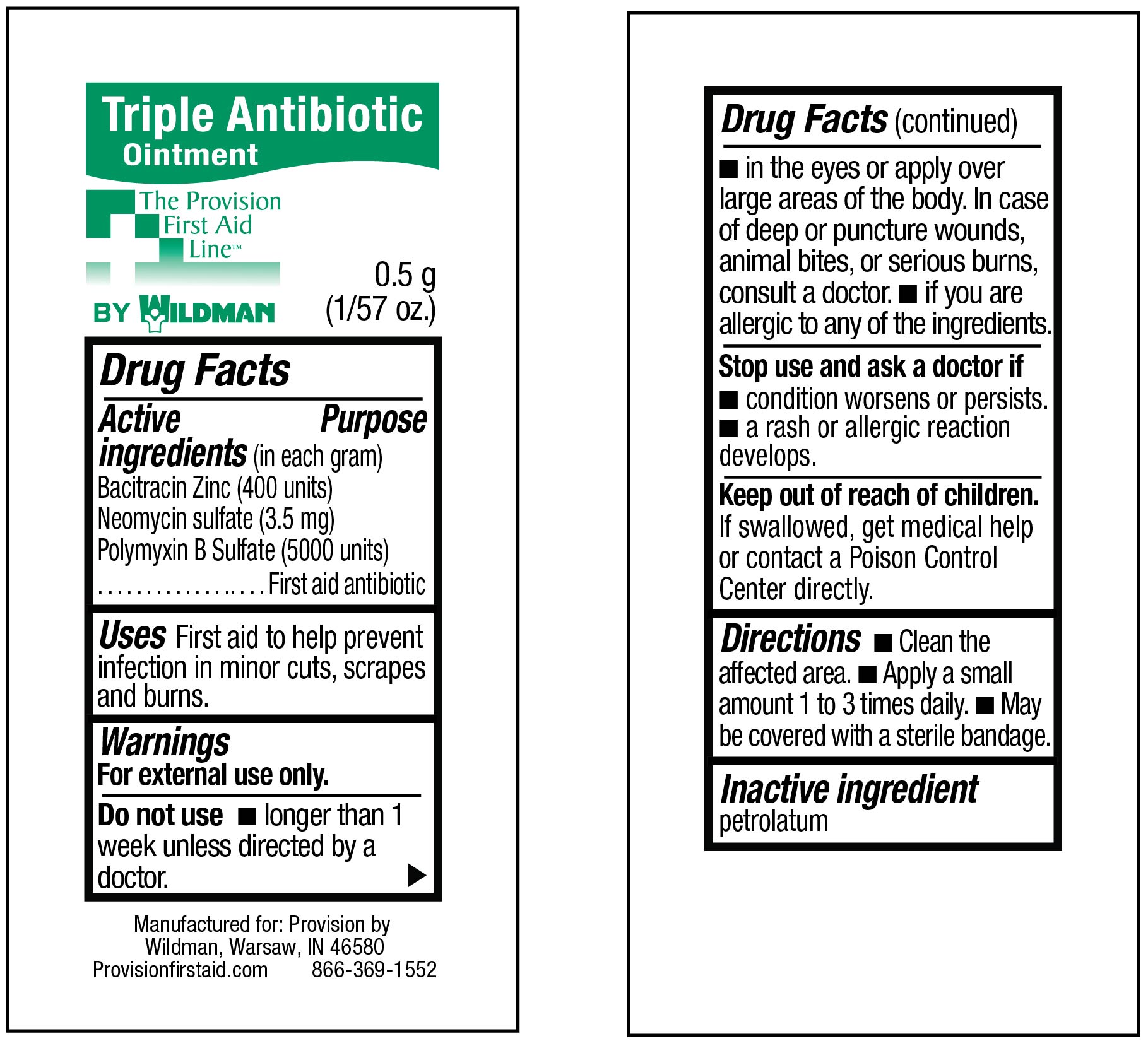 DRUG LABEL: Triple Antibiotic
NDC: 84269-4500 | Form: OINTMENT
Manufacturer: Wildeman Business Group
Category: otc | Type: HUMAN OTC DRUG LABEL
Date: 20240813

ACTIVE INGREDIENTS: BACITRACIN ZINC 400 [iU]/1 g; NEOMYCIN SULFATE 3.5 mg/1 g; POLYMYXIN B SULFATE 5000 [iU]/1 g
INACTIVE INGREDIENTS: PETROLATUM

69103-5603. Triple Antibiotic

Active ingredients

(in each gram)

Bacitracin Zinc (400 units Bacitracin)

Neomycin sulfate (3.5 mg Neomycin)

Polymyxin B Sulfate (Polymyxin B 5000 units)

Purpose

First aid antibiotic

Uses

first aid to help prevent infection in minor cuts, scrapes and burns

Warnings

For external use only

Do not use

- internally
- in eyes
- over large areas of the body or on puncture wounds, animal bites or serious burns
- for more than 1 week unless directed by a doctor
- if you are allergic to any of the ingredients

Stop use and ask a doctor if

- a rash or allergic reaction develops
- condition worsens or persists

Keep out of reach of children

If ingested, contact a Poison Control Center right away.

Directions

- clean affected area
- apply a small amount 1 to 3 times daily
- may cover with a sterile bandage

Inactive ingredient

petrolatum

Principal Display Panel – 0.5g Pouch Label

Triple Antibiotic
Ointment

The Provision
First Aid
Line™

0.5 g
(1/57 oz.)